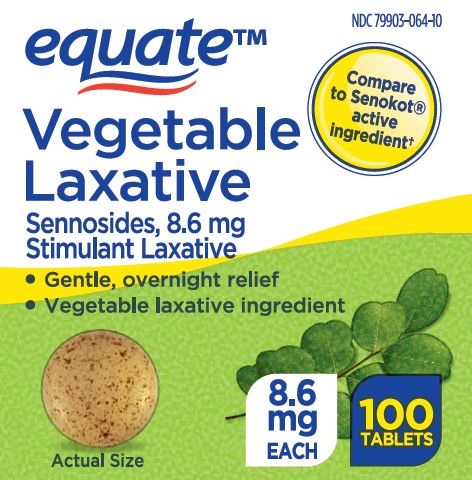 DRUG LABEL: Vegetable Laxative
NDC: 79903-064 | Form: TABLET
Manufacturer: Wal-Mart Stores Inc
Category: otc | Type: HUMAN OTC DRUG LABEL
Date: 20260127

ACTIVE INGREDIENTS: SENNOSIDES 8.6 mg/1 1
INACTIVE INGREDIENTS: SILICON DIOXIDE; CROSCARMELLOSE SODIUM; ANHYDROUS DIBASIC CALCIUM PHOSPHATE; HYPROMELLOSE, UNSPECIFIED; MINERAL OIL; MAGNESIUM STEARATE; CELLULOSE, MICROCRYSTALLINE; MALTODEXTRIN; WATER; SODIUM LAURYL SULFATE; STEARIC ACID

Vegetable Laxative Tablets

Drug Facts

Active ingredient (in each tablet)

Sennosides 8.6 mg

Purpose

Laxative

Uses

- relieves occasional constipation (irregularity)
- generally produces bowel movement in 6-12 hours

Warnings

Do not use

- laxative products for longer than 1 week, unless directed by a doctor

Ask a doctor before use if you have

- stomach pain
- nausea
- vomiting
- noticed a sudden change in bowel habits that lasts over 2 weeks

Stop use and ask a doctor if you have rectal bleeding or fail to have a bowel movement after use of a laxative. These may indicate a serious condition.

PREGNANCY OR BREAST FEEDING

If pregnant or breast-feeding, ask a health professional before use.

Keep out of reach of children. In case of overdose, get medical help or contact a Poison Control Center right away.

Directions

Age | Starting Dosage | Maximum Dosage
adults and children 12 years of age or over | 2 tablets once a day | 4 tablets twice a day
children 6 to under 12 years | 1 tablet once a day | 2 tablets twice a day
children 2 to under 6 years | 1/2 tablet once a day | 1 tablet twice a day
children under 2 years | ask a doctor | ask a doctor

Other information

- each tablet contains: calcium 25 mg and sodium 3 mg Very Low Sodium
- store at 25°C (77°F); excursions permitted between 15°-30°C (59°-86°F)

Inactive ingredients

Colloidal silicon dioxide, croscarmellose sodium, dicalcium phosphate, hypromellose, liquid paraffin, magnesium stearate, microcrystalline cellulose, maltodextrin, purified water, sodium lauryl sulphate, stearic acid

Questions or comments?

Call 1-888-287-1915

PRINCIPAL DISPLAY PANEL

Vegetable Laxative

Sennosides USP, 8.6 mg
Stimulant Laxative
Gentle, Overnight Relief
Vegetable Laxative Ingredient

100 TABLETS